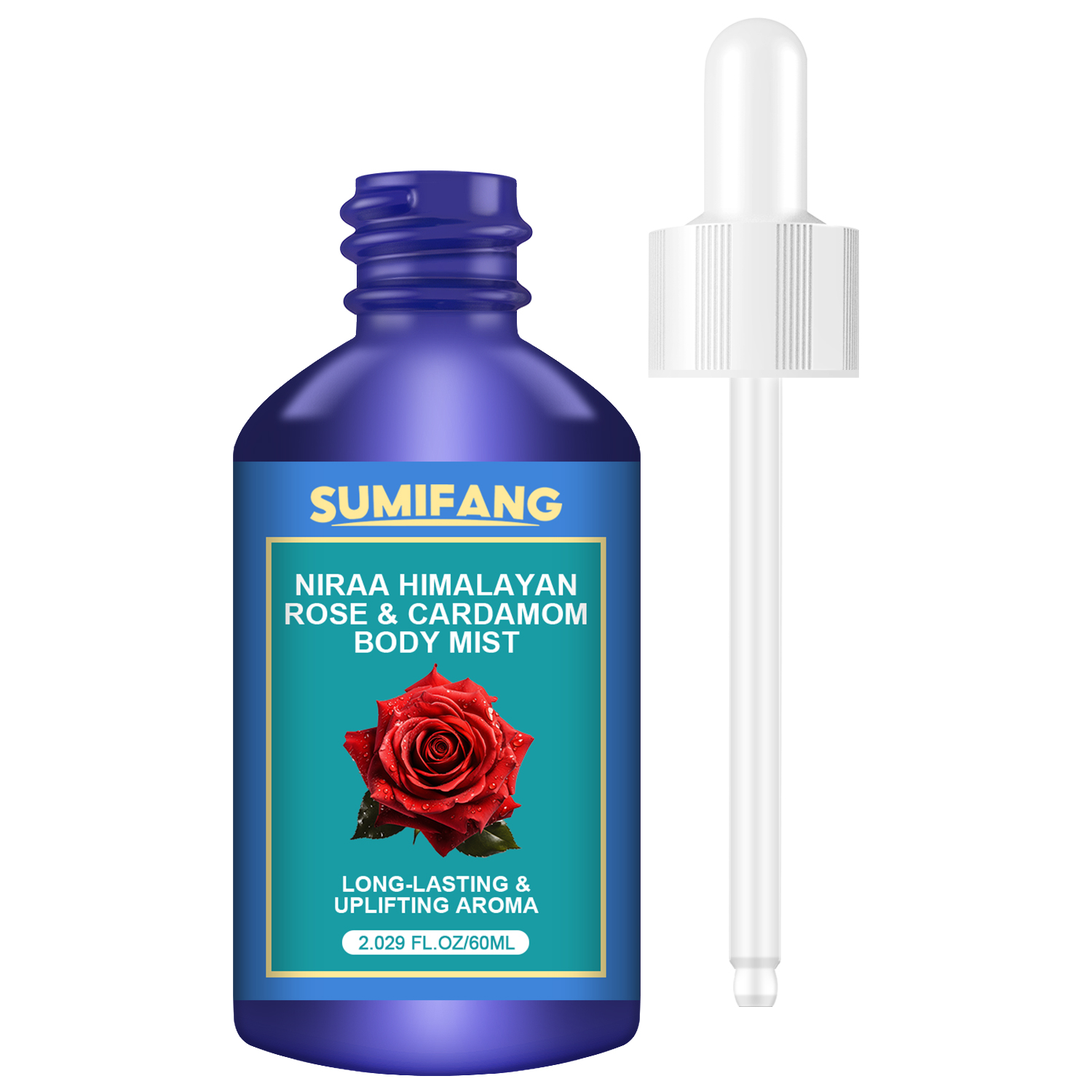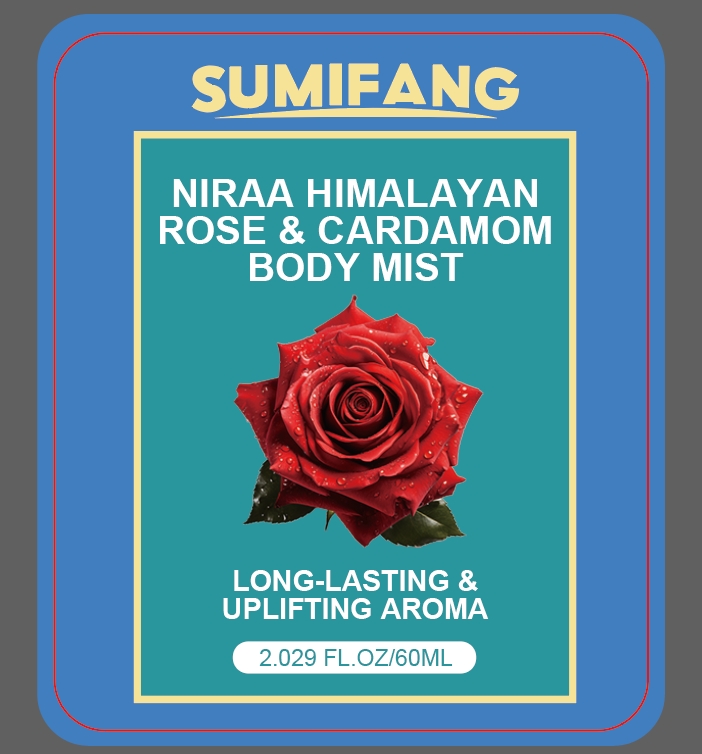 DRUG LABEL: ROSE CARDAMOMBODY MIST
NDC: 84025-104 | Form: LIQUID
Manufacturer: Guangzhou Yanxi Biotechnology Co.. Ltd
Category: otc | Type: HUMAN OTC DRUG LABEL
Date: 20240731

ACTIVE INGREDIENTS: 1,2-BUTANEDIOL 5 mg/60 mL; ALLANTOIN 3 mg/60 mL
INACTIVE INGREDIENTS: WATER

DOSAGE AND ADMINISTRATION

Essential oils for massage and skin care

WARNINGS

Keep out of children

INACTIVE INGREDIENT

Aqua

INDICATIONS AND USAGE

For daily skin care

Keep out of children

PURPOSE

Moisturizes and smoothes the skin